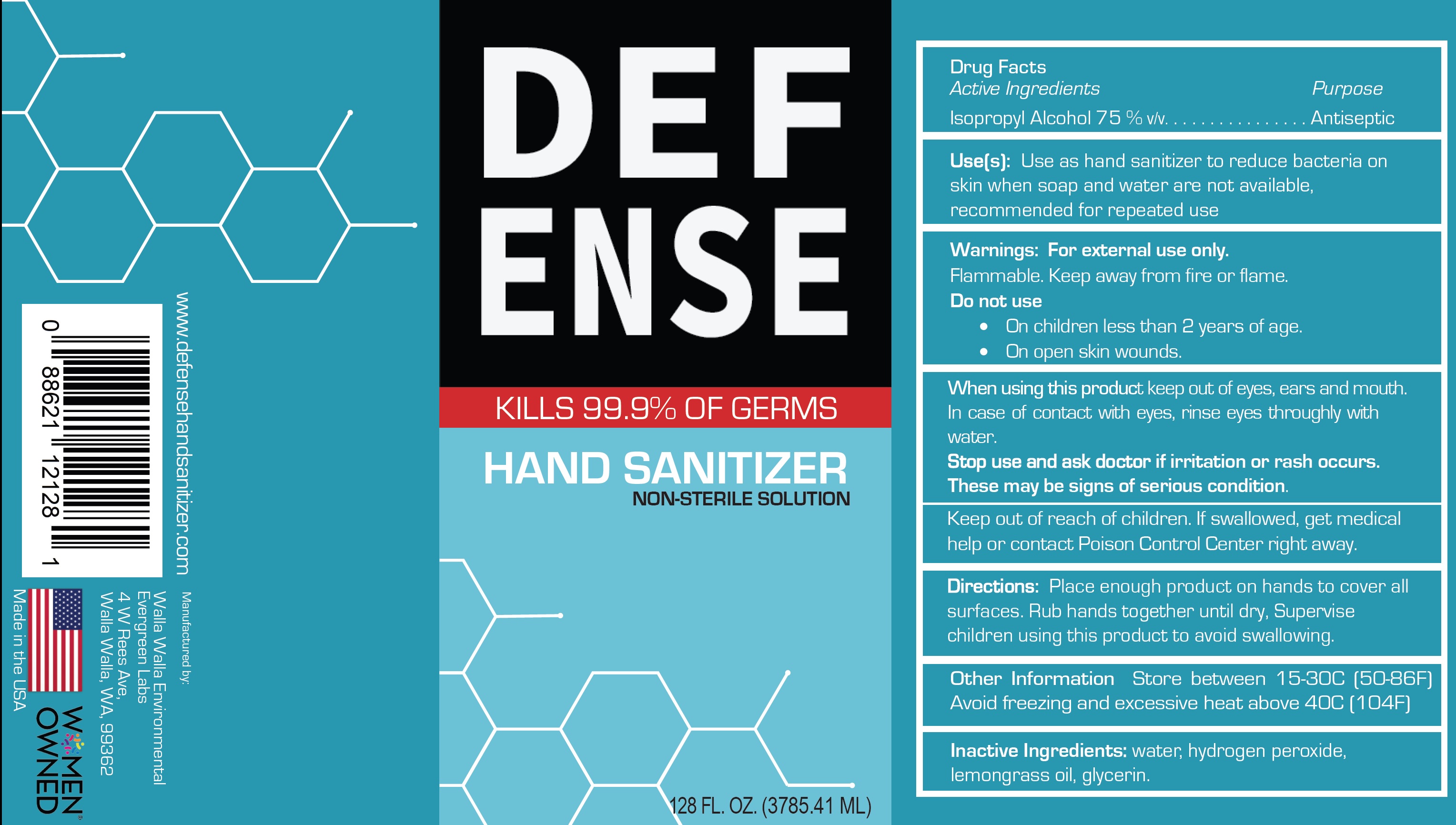 DRUG LABEL: DEFENSE Hand Sanitizer
NDC: 80579-001 | Form: LIQUID
Manufacturer: Walla Walla Environmental, Inc.
Category: otc | Type: HUMAN OTC DRUG LABEL
Date: 20220831

ACTIVE INGREDIENTS: ISOPROPYL ALCOHOL 0.75 mL/1 mL
INACTIVE INGREDIENTS: WATER; HYDROGEN PEROXIDE; WEST INDIAN LEMONGRASS OIL; GLYCERIN

DEFENSE Hand Sanitizer

Active Ingredients

Isopropyl Alcohol 75% v/v

Purpose

Antiseptic

Use[s]:

Use as hand sanitizer to reduce bacteria on skin when soap and water are not available, recommended for repeated use

Warnings:

For external use only.

Flammable. Keep away from fire or flame.

Do not use

- On children less than 2 years of age.
- On open skin wounds.

When using this product

keep out of eyes, ears, and mouth. In case of contact with eyes, rinse eyes thoroughly with water.

Stop use and ask a doctor

if irritation or rash occurs. These may be signs of a serious condition.

Keep out of reach of children.

If swallowed, get medical help or contact a Poison Control Center right away.

Directions:

• Place enough product on hands to cover all surfaces. Rub hands together until dry,
• Supervise children using this product to avoid swallowing.

Other Information

- Store between 15-30C [50-86F]
- Avoid freezing and excessive heat above 40C [104F]

Inactive Ingredients:

water, hydrogen peroxide, lemongrass oil, glycerin.